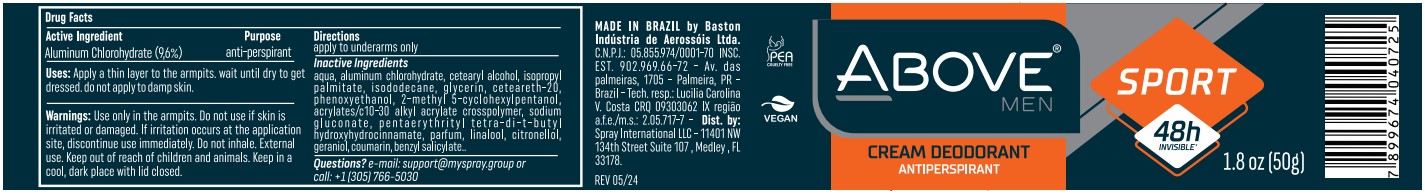 DRUG LABEL: ABOVE CLASSIC MEN SPORT ANTIPERSPIRANT DEODORANT 48H
NDC: 73306-1174 | Form: CREAM
Manufacturer: BASTON INDUSTRIA DE AEROSSOIS LTDA
Category: otc | Type: HUMAN OTC DRUG LABEL
Date: 20240519

ACTIVE INGREDIENTS: ALUMINUM CHLOROHYDRATE 9.6 mg/100 g
INACTIVE INGREDIENTS: ISOPROPYL PALMITATE

ABOVE CLASSIC MEN SPORT ANTIPERSPIRANT DEODORANT 48H CREAM

ALUMINUM CHLOROHYDRATE (CLOROIDRÓXIDO DE ALUMÍNIO) 9.6%

UNDERARM ANTIPERSPIRANT

APPLY A THIN LAYER TO ARMPITS. WAIT FOR IT TO DRY BEFORE GETTING DRESSED. DO NOT APPLY ON WET SKIN

SUPPORT@MYSPRAY.GROUP OR CALL 305 766-5030

USE ONLY ON ARMPITS. DO NOT USE IF SKIN IS IRRITATED OR INJURED IF IRRITATION OCCURS AT THE SITE OF APPLICATION, DISCONTINUE USE IMMEDIATELY. DO NOT INGEST. EXTERNAL USE. KEEP AWAY FROM CHILDREN AND ANIMALS.

USE ONLY ON ARMPITS. DO NOT USE IF SKIN IS IRRITATED
OR INJURED IF IRRITATION OCCURS AT THE SITE OF APPLICATION, DISCONTINUE USE IMMEDIATELY.
DO NOT INGEST. EXTERNAL USE.
KEEP AWAY FROM CHILDREN AND ANIMALS.

KEEP OUT OF REACH OF CHILDREN

USE ONLY ON ARMPITS. DO NOT USE IF SKIN IS IRRITATED

USE ONLY ON ARMPITS. DO NOT USE IF SKIN IS IRRITATED OR INJURED IF IRRITATION OCCURS AT THE SITE OF APPLICATION, DISCONTINUE USE IMMEDIATELY. DO NOT INGEST. EXTERNAL USE. KEEP AWAY FROM CHILDREN AND ANIMALS.

USE ONLY ON ARMPITS. DO NOT USE IF SKIN IS IRRITATED
OR INJURED IF IRRITATION OCCURS AT THE SITE OF APPLICATION, DISCONTINUE USE IMMEDIATELY.
DO NOT INGEST. EXTERNAL USE.
KEEP AWAY FROM CHILDREN AND ANIMALS.

AQUA (ÁGUA) CETEARYL ALCOHOL (ÁLCOOL CETEARÍLICO) ISOPROPYL PALMITATE (PALMITATO DE ISOPROPILA) ISODODECANE (ISODODECANO) GLYCERIN (GLICEROL) CETEARETH-20 (CETEARETE-20) PARFUM (PERFUME) PHENOXYETHANOL (FENOXIETANOL) 2-METHYL 5-CYCLOHEXYLPENTANOL (2-METIL 5-CICLOEXILPENTANOL) ACRYLATES/C10-30 ALKYL ACRYLATE CROSSPOLYMER (CROSPOLÍMERO DE ACRILATOS/ACRILATO DE ALQUILA C10-30) SODIUM GLUCONATE (GLICONATO DE SÓDIO) PENTAERYTHRITYL TETRA-DI-T-BUTYL HYDROXYHYDROCINNAMATE (PENTAERITRITIL TETRA-DI-T-BUTIL HIDROXI-HIDROCINAMATO)

AQUA (ÁGUA)
CETEARYL ALCOHOL (ÁLCOOL CETEARÍLICO)
ISOPROPYL PALMITATE (PALMITATO DE ISOPROPILA)
ISODODECANE (ISODODECANO)
GLYCERIN (GLICEROL)
CETEARETH-20 (CETEARETE-20)
PARFUM (PERFUME)
PHENOXYETHANOL (FENOXIETANOL)
2-METHYL 5-CYCLOHEXYLPENTANOL (2-METIL 5-CICLOEXILPENTANOL)
ACRYLATES/C10-30 ALKYL ACRYLATE CROSSPOLYMER (CROSPOLÍMERO DE ACRILATOS/ACRILATO DE ALQUILA C10-30)
SODIUM GLUCONATE (GLICONATO DE SÓDIO)
PENTAERYTHRITYL TETRA-DI-T-BUTYL HYDROXYHYDROCINNAMATE (PENTAERITRITIL TETRA-DI-T-BUTIL HIDROXI-HIDROCINAMATO)